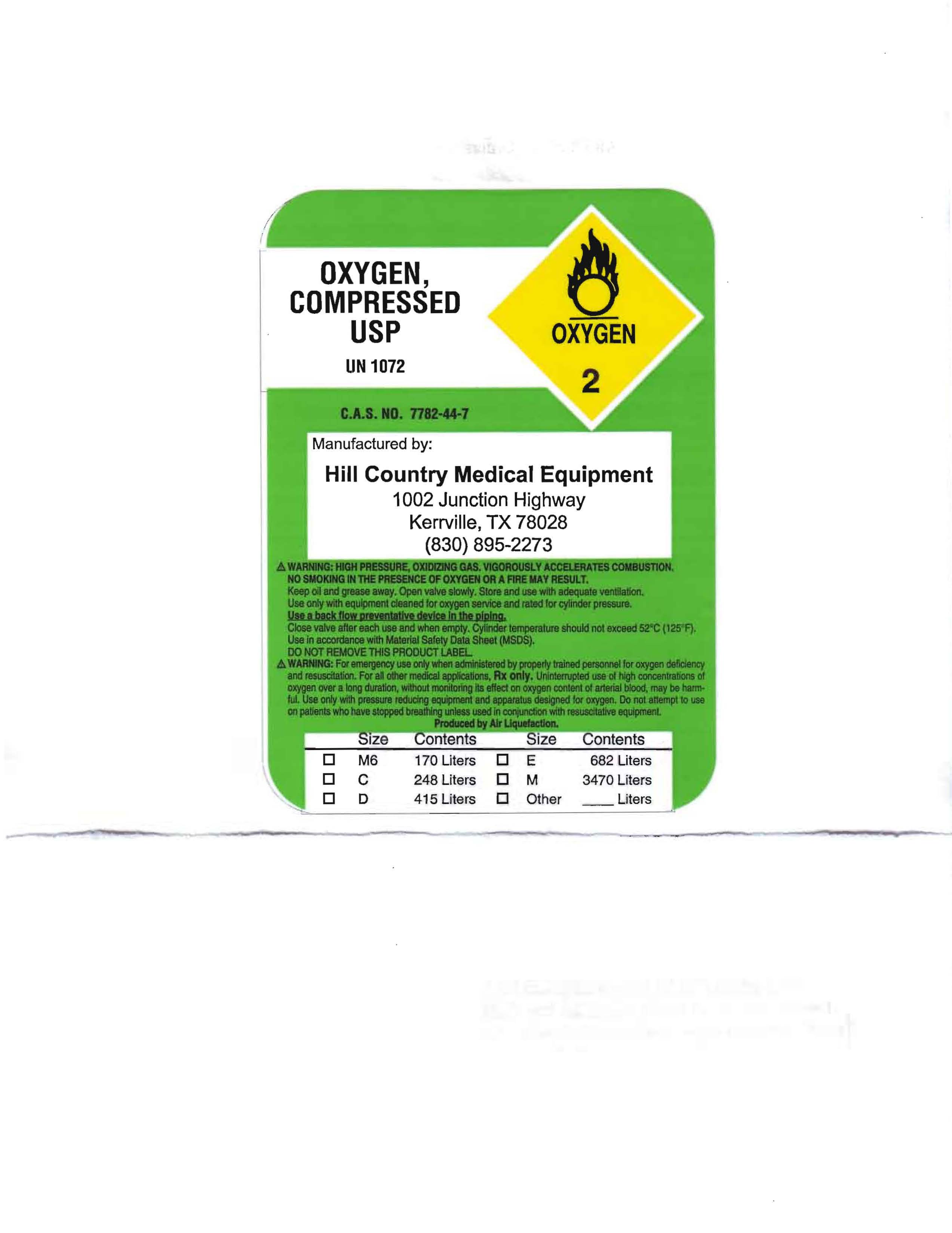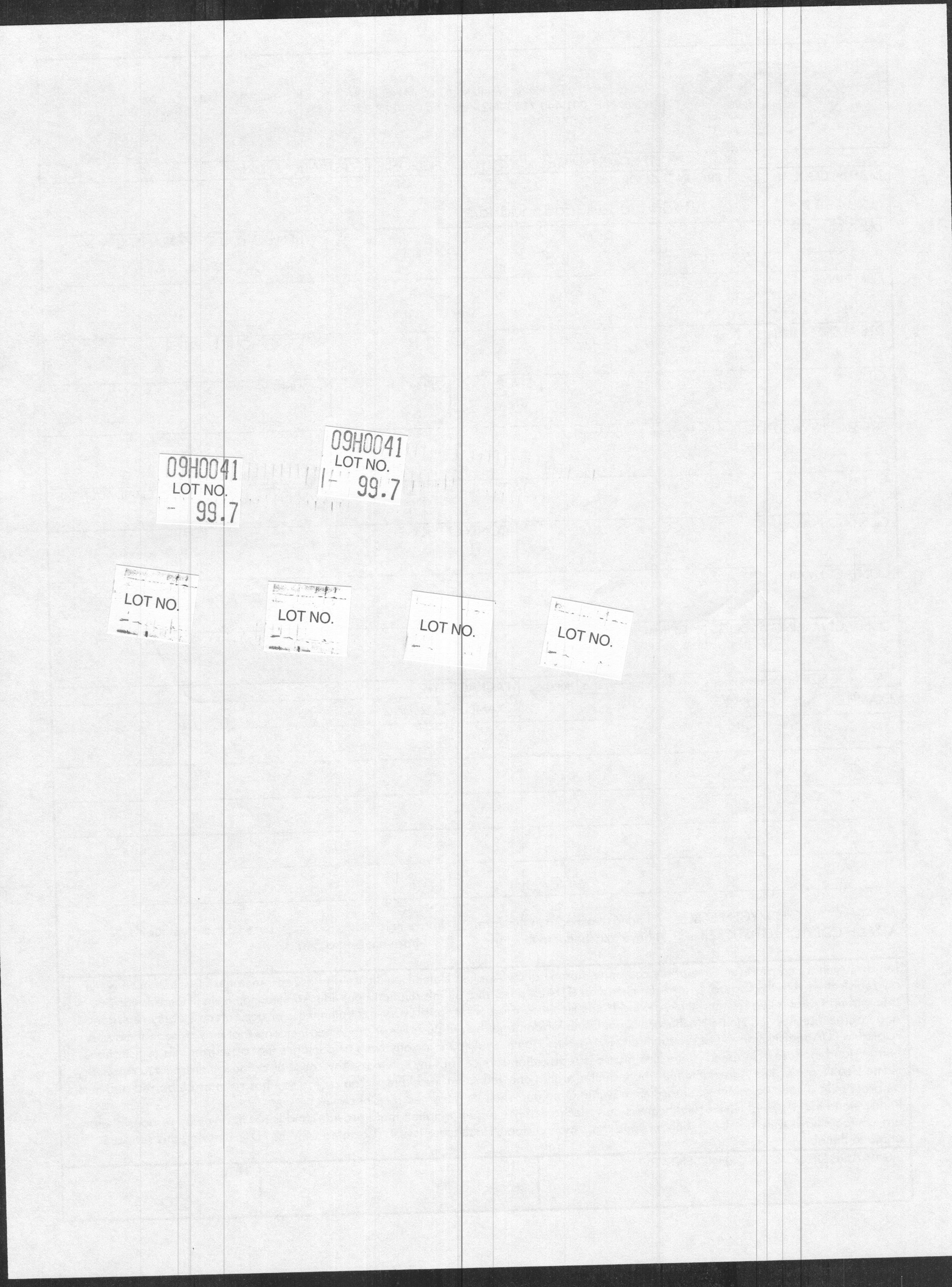 DRUG LABEL: OXYGEN
NDC: 59972-0106 | Form: GAS
Manufacturer: Hill Country Medical
Category: prescription | Type: HUMAN PRESCRIPTION DRUG LABEL
Date: 20090828

ACTIVE INGREDIENTS: OXYGEN 99 L/100 L

OXYGEN